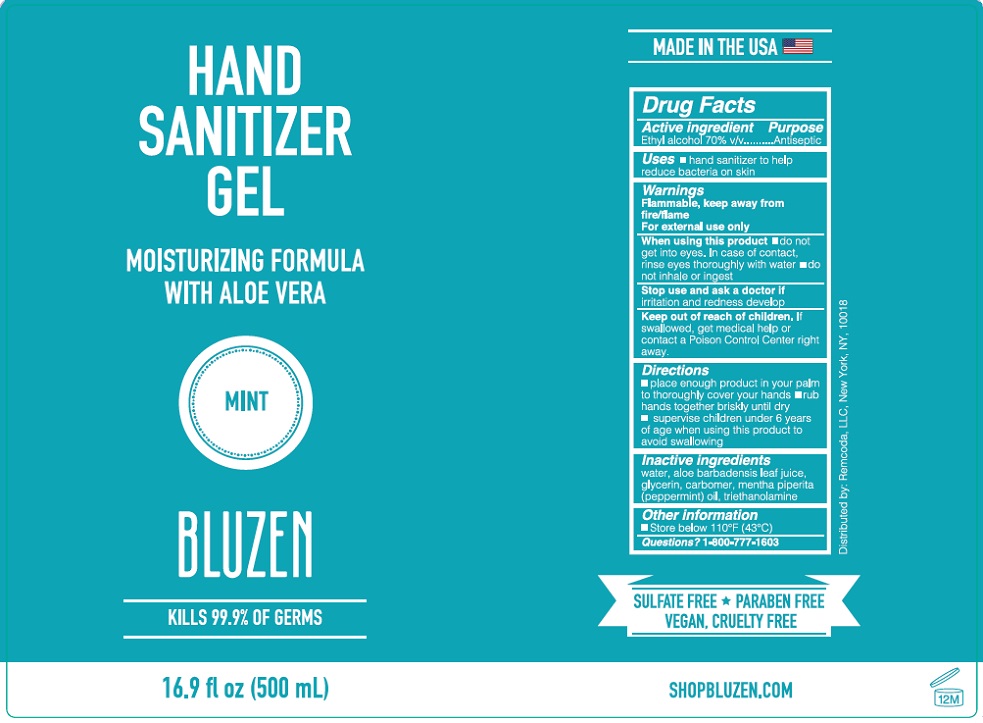 DRUG LABEL: BluZen Hand Sanitizer
NDC: 79200-102 | Form: GEL
Manufacturer: Remcoda, Llc
Category: otc | Type: HUMAN OTC DRUG LABEL
Date: 20200701

ACTIVE INGREDIENTS: ALCOHOL 70 mL/100 mL
INACTIVE INGREDIENTS: WATER; ALOE VERA LEAF; GLYCERIN; CARBOMER HOMOPOLYMER, UNSPECIFIED TYPE; PEPPERMINT OIL; TROLAMINE

BLUZEN HAND SANITIZER GEL

Active ingredient

Ethyl alcohol 70% v/v

Purpose

Antiseptic

INDICATIONS AND USAGE

Uses ▪ hand sanitizer to help reduce bacteria on skin.

Warnings

Flammable, keep away from fire/flame.

For external use only.

When using this product ▪ do not get into eyes. In case of contact, rinse eyes thoroughly with water.

▪ do not inhale or ingest.

Stop use and ask a doctor if irritation and redness develop

Keep out of reach of children. If swallowed, get medical help or contact a Poison Control Center right away

Directions

▪ place enough product in your palm to thoroughly cover your hands ▪ rub hands together briskly until dry

▪ supervise children under 6 years of age when using this product to avoid swallowing.

Other information

▪ Store below 110°F (43°C)

Inactive ingredients

water, aloe barbadensis leaf juice, glycerin, carbomer, mentha piperita (peppermint) oil, triethanolamine

Questions? 1-800-777-1603

MOISTURIZING FORMULA WITH ALOE VERA

MINT

KILLS 99.9% OF GERMS

MADE IN THE USA

SULFATE FREE * PARABEN FREE

VEGAN, CRUELTY FREE

SHOPBLUZEN.COM

Distributed by: Remcoda, LLC, New York, NY, 10018